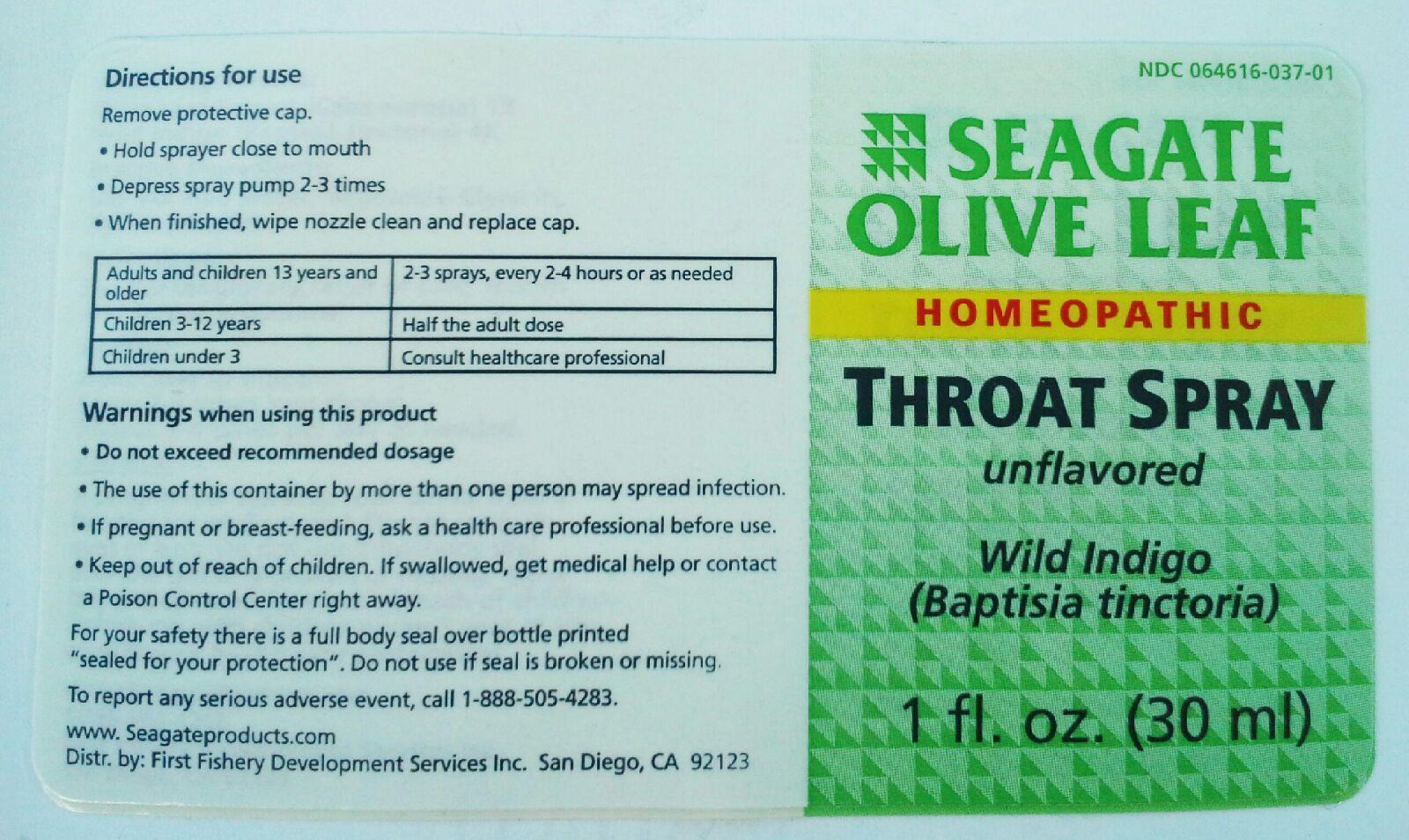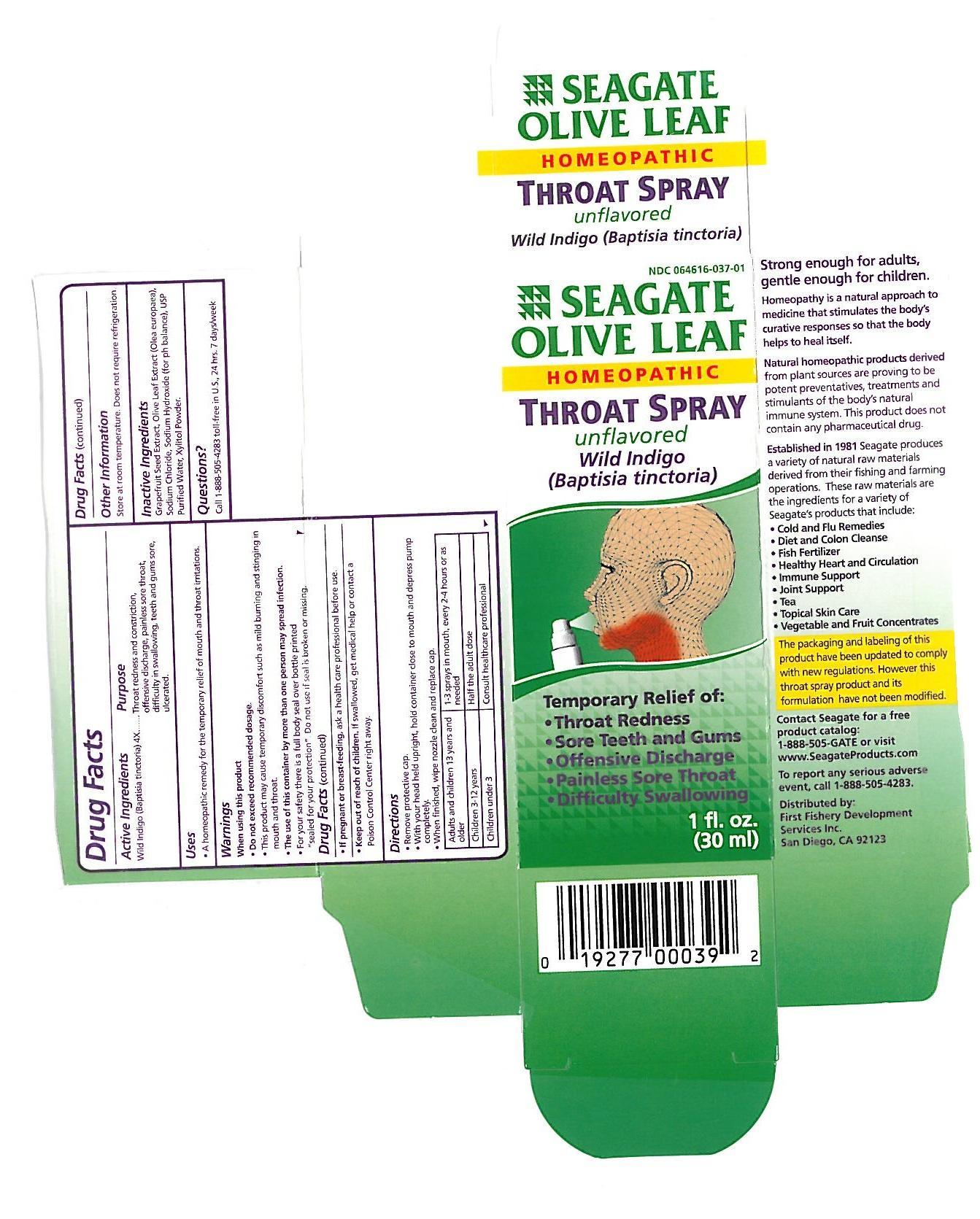 DRUG LABEL: Olive Leaf Throat
NDC: 64616-037 | Form: SPRAY
Manufacturer: Vitality Works, Inc.
Category: homeopathic | Type: HUMAN PRESCRIPTION DRUG LABEL
Date: 20140520

ACTIVE INGREDIENTS: BAPTISIA TINCTORIA 4 [hp_X]/1 mL
INACTIVE INGREDIENTS: OLEA EUROPAEA LEAF; Xylitol; GLYCERIN; WATER

Olive Leaf Throat Spray

Wild Indigo (Baptisia tinctoria) 4X

Olive Leaf Throat Spray

Olive Leaf Extract (Olea europaea), Glycerin, USP Purified Water, Xylitol.

Olive Leaf Throat Spray

Do not exceed recommended dosage. This product may cause temporary discomfort such as mild burning and stinging in mouth and throat. The use of this container by more than one person may spread infection. For you safety there is a full body seal over bottle printed "sealed for your protection". Do not use if seal is broken or missing. If pregnant or breast feeding, ask a health care professional before use.

Olive Leaf Throat Spray

Keep out of reach of children. If swallowed, get medical help or contact a Poison Control Center right away.

Olive Leaf Throat Spray

A homeopathic remedy for the temporary relief of mouth and throat irritations.

Olive Leaf Throat Spray

Remove protective cap. With you head held upright, hold container close to mouth and depress pump completely. When finished, wipe nozzle clean and replace cap.

Adults and children 13 years and older - 1-3 sprays in mouth, every 2-4 hours or as needed.

Children 3-12 years - Half the adult dose.

Childern under 3 - Consult health care professional.

Olive Leaf Throat Spray

Wild Indigo (Baptisia tinctoria) - relieves redness and constriction, offensive discharge, painless sore throat, difficulty in swallowing, teeth and gums sore, ulcerated.